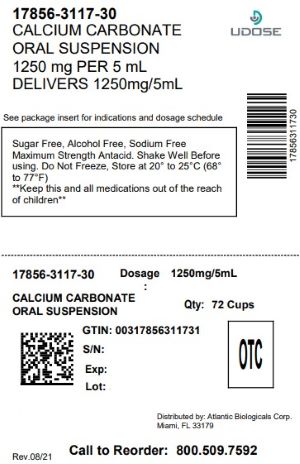 DRUG LABEL: Calcium Carbonate
NDC: 17856-3117 | Form: SUSPENSION
Manufacturer: Atlantic Biologicals Corps
Category: otc | Type: HUMAN OTC DRUG LABEL
Date: 20250512

ACTIVE INGREDIENTS: CALCIUM CARBONATE 1250 mg/5 mL
INACTIVE INGREDIENTS: PROPYLPARABEN; METHYLPARABEN; PROPYLENE GLYCOL; SORBITOL; GLYCERIN; XANTHAN GUM; CITRIC ACID MONOHYDRATE; FD&C RED NO. 40; D&C RED NO. 33; SACCHARIN CALCIUM; WATER

Calcium Carbonate

DRUG FACTS

Active ingredient (in each 5 mL teaspoonful)

Calcium Carbonate 1250 mg (Equivalent to 500 mg elemental Calcium)

Purpose

Antacid

Uses

relieves:

- heartburn
- acid indigestion
- sour stomach
- upset stomach associated with these symptoms

Warnings

Ask a doctor or pharmacist before use if you aretaking a prescription drug. Antacids may interact with certain prescription drugs.

When using this product,do not take more than 6 teaspoonfuls (30 mL) in a 24-hour period or use the maximum dosage for more than 2 weeks.

Keep out of reach of children.

Directions

- Shake well before using.
- Take 1 to 2 teaspoonfuls (5 to 10 mL) as symptoms occur, or as directed by a doctor.

Other information

- store at 20° to 25°C (68° to 77°F)
- do not freeze
- packaged with tamper evident seal

Inactive ingredients

calcium saccharin, citric acid, D&C Red No. 33, FD&C Red No. 40, flavoring, glycerin, methylparaben, propylene glycol, propylparaben, purified water, sorbitol and xanthan gum.

Questions?

Call 1-800-845-8210.